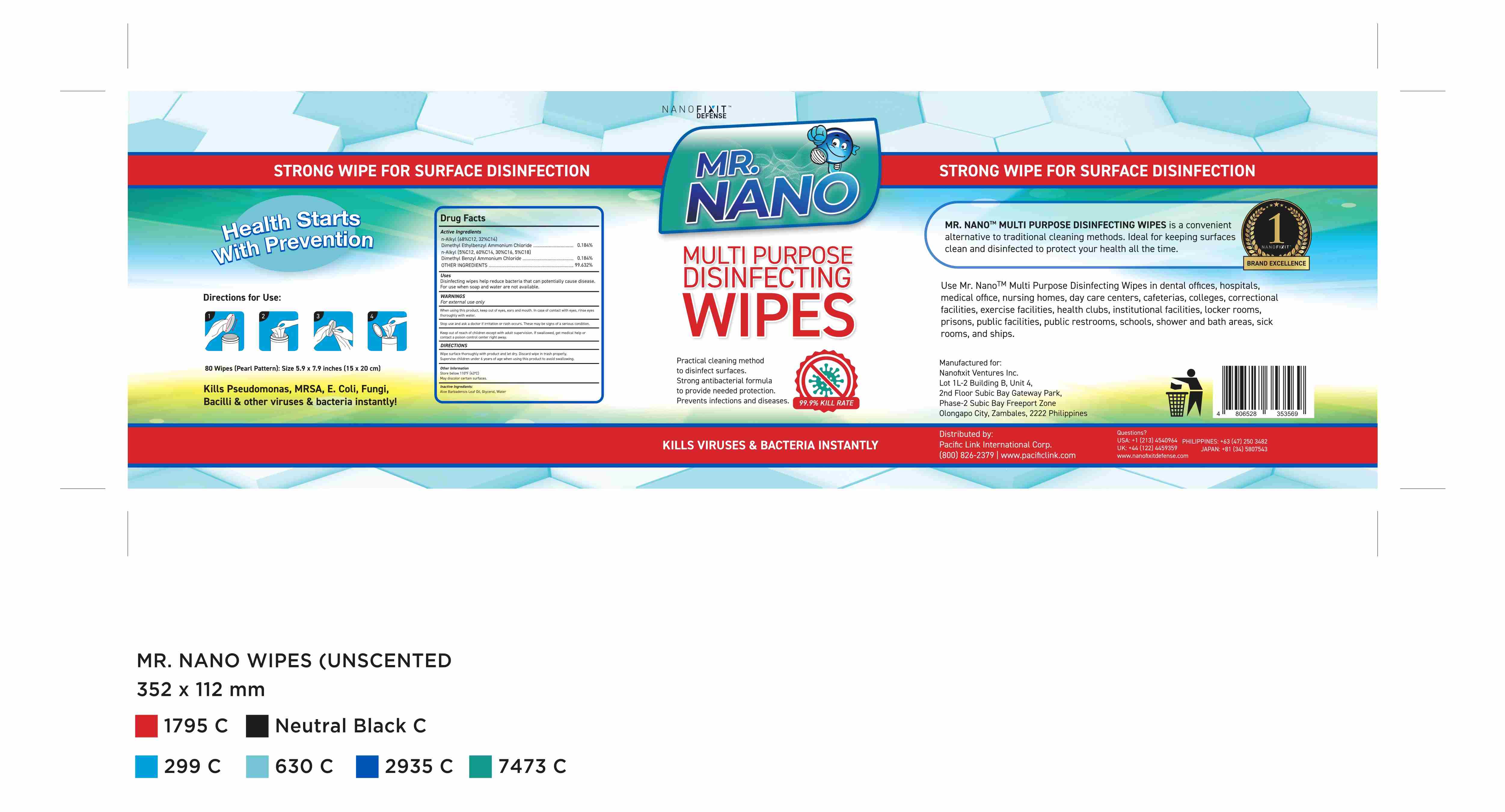 DRUG LABEL: Disinfecting Wipes
NDC: 92763-010 | Form: CLOTH
Manufacturer: NANOFIXIT VENTURES INC.	
Category: otc | Type: HUMAN OTC DRUG LABEL
Date: 20200904

ACTIVE INGREDIENTS: N-ALKYL ETHYLBENZYL DIMETHYL AMMONIUM CHLORIDE (C12-C14) 1 g/80 1; N-ALKYL DIMETHYL BENZYL AMMONIUM CHLORIDE (C12-C18) 1 g/80 1
INACTIVE INGREDIENTS: WATER; PHENOXYETHANOL; GREEN TEA LEAF; PROPYLENE GLYCOL

DOSAGE AND ADMINISTRATION

Store below 110°F(43°C)

INACTIVE INGREDIENT

AQUA

PROPYLENE GLYCOL

PHENOXYETHANOL

GREEN TEA EXTRACT

INDICATIONS AND USAGE

Wipe surface thoroughly with product and let dry.Discard wipe in trash properly.Supervise children under 6 years of age when using this product to avoid swallowing.

ACTIVE INGREDIENT

n-Alkyl(68%C12,32%C14) dimethyl ethylbenzyl ammonium chloride

n-Alkyl(5%C12,60%C14,30%C16,5%C18) dimethyl benzyl ammonium chloride

Keep out of reach of children except with adult supervision. If swallowed, get medical help or contact a poison control center right away.

PURPOSE

Disinfection
Sterilization
No Rinseing

WARNINGS

For external use only.When using this product, keep out of eyes,ears and mouth. In case of contact with eyes, rinse eyes thoroughly with water.